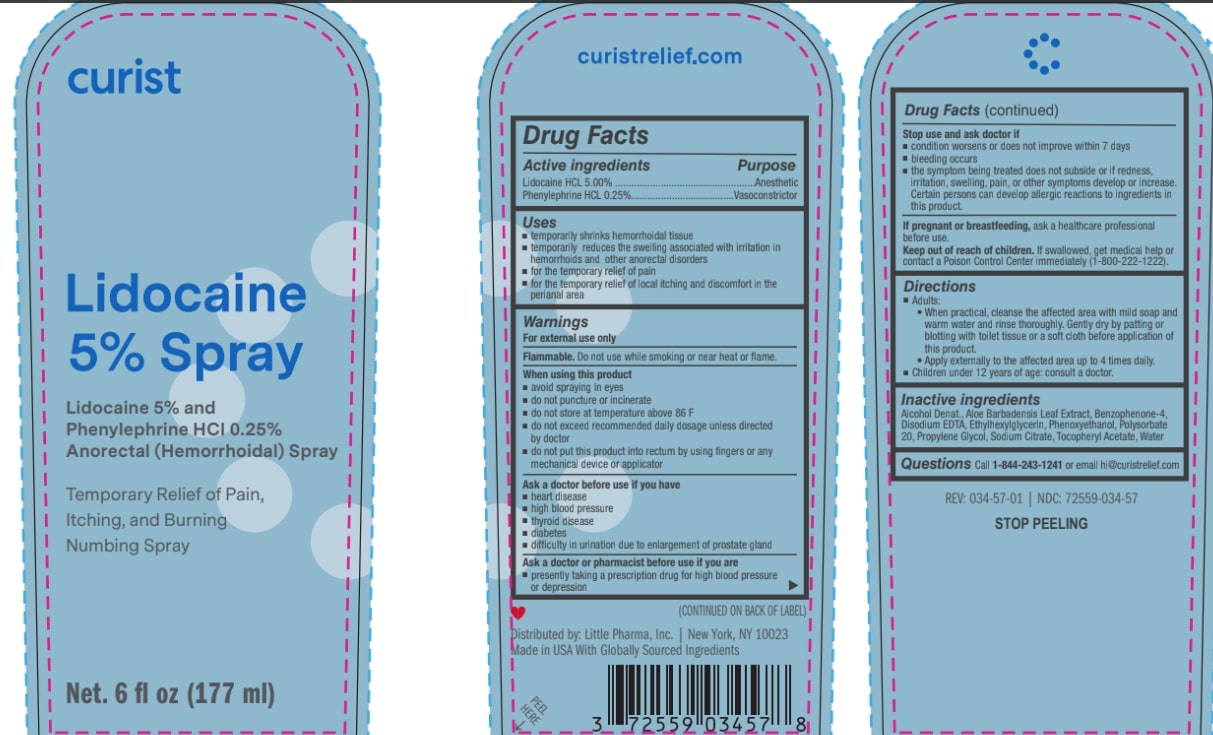 DRUG LABEL: Curist 5% Lidocaine
NDC: 72559-034 | Form: SPRAY
Manufacturer: Little Pharma, Inc.
Category: otc | Type: HUMAN OTC DRUG LABEL
Date: 20250616

ACTIVE INGREDIENTS: LIDOCAINE HYDROCHLORIDE 500 g/100 mL; PHENYLEPHRINE HYDROCHLORIDE 25 g/100 mL
INACTIVE INGREDIENTS: WATER; SODIUM CITRATE; DEHYDRATED ALCOHOL; BENZOPHENONE-4; EDETATE DISODIUM; ETHYLHEXYLGLYCERIN; POLYSORBATE 20; .ALPHA.-TOCOPHEROL ACETATE; ALOE VERA LEAF; PHENOXYETHANOL; PROPYLENE GLYCOL

Curist Lidocaine 5% Spray

Active ingredient

Lidocaine 5%

Phenylephrine HCL 0.25%

Purpose

Anorectal (hemorrhoidal) spray

Uses

- temporarily shrinks hemorrhoidal tissue
  ■ temporarily reduces the swelling associated with irritation in
  hemorrhoids and other anorectal disorders
  ■ for the temporary relief of pain
  ■ for the temporary relief of local itching and discomfort in the
  perianal area

Warnings

For external use only

Flamable, Do not use while smoking or near heat ot flame

When using this product
■ avoid spraying in eyes
■ do not puncture or incinerate
■ do not store at temperature above 86 F
■ do not exceed recommended daily dosage unless directed
by doctor
■ do not put this product into rectum by using fingers or any
mechanical device or applicator
Ask a doctor before use if you have
■ heart disease
■ high blood pressure
■ thyroid disease
■ diabetes
■ difficulty in urination due to enlargement of prostate gland
Ask a doctor or pharmacist before use if you are
■ presently taking a prescription drug for high blood pressure
or depression

Stop use and ask doctor if
■ condition worsens or does not improve within 7 days
■ bleeding occurs
■ the symptom being treated does not subside or if redness,
irritation, swelling, pain, or other symptoms develop or increase.
Certain persons can develop allergic reactions to ingredients in
this product.

If pregnant or breastfeeding, ask a healthcare professional
before use.
Keep out of reach of children. If swallowed, get medical help or
contact a Poison Control Center immediately (1-800-222-1222).

When using this product

- avoid contact with eyes
- do not exceed recommended dosage unless directed by a doctor
- do not put this product into the rectum by using fingers or any mechanical device or applicator

Stop use and ask a doctor if

- rectal bleeding occurs
- condition worsens or does not improve within 7 days
- allergic reaction occurs to ingredients in this product
- sumptom being treated does not subside or if redness, irritation, swelling, pain or other symptoms develop or increase

PREGNANCY OR BREAST FEEDING

If pregnant or breastfeeding, ask a health professional before use

Keep out of reach of children.If swallowed, get medical help or contact a Poison Control Center right away

Directions

Adults:
• When practical, cleanse the affected area with mild soap and
warm water and rinse thoroughly. Gently dry by patting or
blotting with toilet tissue or a soft cloth before application of
this product.
• Apply externally to the affected area up to 4 times daily.
■ Children under 12 years of age: consult a doctor.

INACTIVE INGREDIENT

Inactive ingredientsAlcohol Denat., Aloe Barbadensis Leaf Extract, Benzophenone-4,
Disodium EDTA, Ethylhexylglycerin, Phenoxyethanol, Polysorbate
20, Propylene Glycol, Sodium Citrate, Tocopheryl Acetate, Water

QUESTIONS

QuestionsCall 1-844-243-1241or email hi@curistrelief.com

Distributed by:

Little Pharma, Inc. | New York, NY 10023

Made in USA With Globally Sourced Ingredients

PACKAGE LABEL

curist

Lidocaine Spray

5% Spray

Anorectal (Hemorrhoidal) Spray

Temporary Relief of Pain, Itching, and Burning

Numbing Spray

Net Wt. 6 fl oz (177 ml)